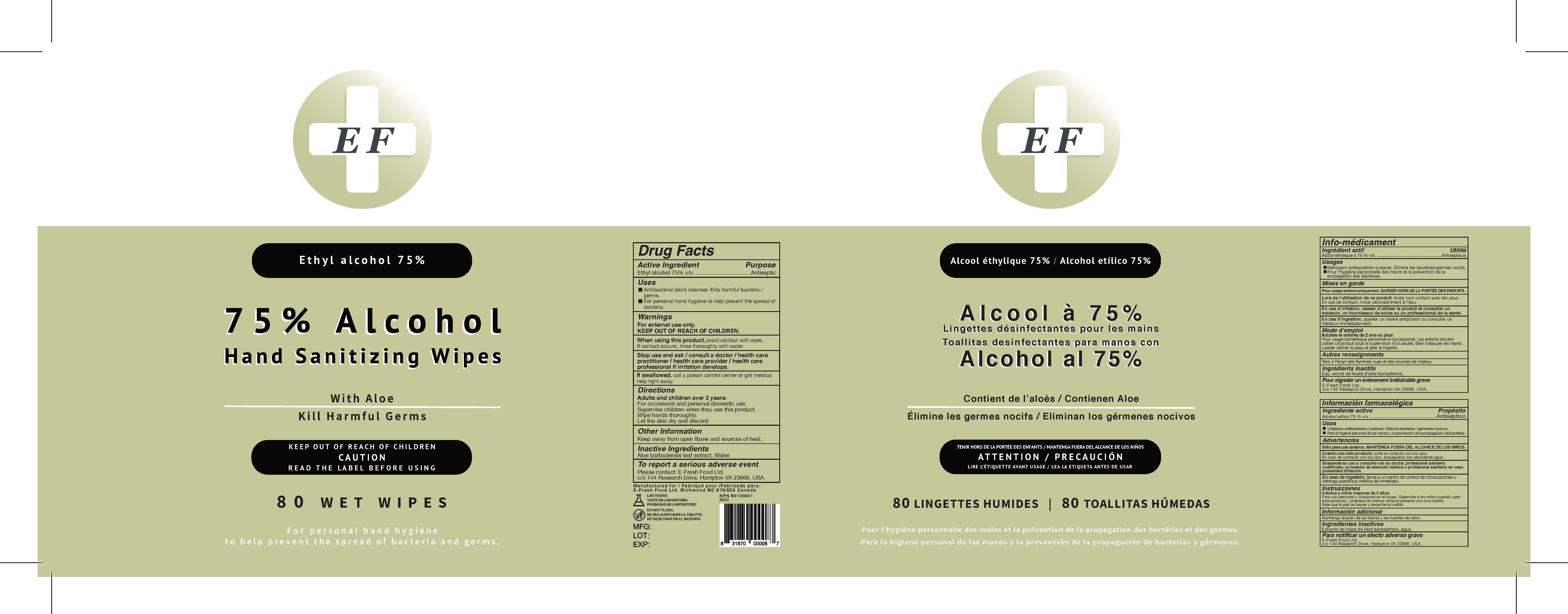 DRUG LABEL: 75% Alcohol Hand Sanitizing Wipes
NDC: 80199-009 | Form: CLOTH
Manufacturer: E-Fresh Food Ltd.
Category: otc | Type: HUMAN OTC DRUG LABEL
Date: 20201015

ACTIVE INGREDIENTS: ALCOHOL 0.75 mL/1 mL
INACTIVE INGREDIENTS: WATER 0.25 mL/1 mL

ACTIVE INGREDIENT

Ethyl alcohol 75% v/v.

PURPOSE

Antiseptic

DOSAGE AND ADMINISTRATION

For external use only.KEEP OUT OF REACH OF CHILDREN.

INACTIVE INGREDIENT

Water

INDICATIONS AND USAGE

Antibacterial (skin) cleanser. Kills harmful bacteria /germs. For personal hand hygiene to help prevent the spread of bacteria.

Adults and children over 2 years:
For occasional and personal domestic use.
Supervise children when they use this product.
Wipe hands thoroughly.
Let the skin dry and discard.

KEEP OUT OF REACH OF CHILDREN.

WARNINGS

For external use only.
KEEP OUT OF REACH OF CHILDREN

PACKAGE LABEL

80wipe NDC:80199-009-01